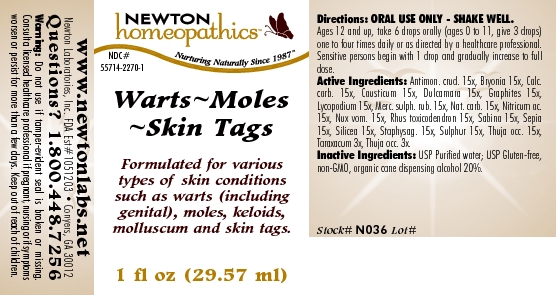 DRUG LABEL: Warts - Moles - Skin Tags 
NDC: 55714-2270 | Form: LIQUID
Manufacturer: Newton Laboratories, Inc.
Category: homeopathic | Type: HUMAN OTC DRUG LABEL
Date: 20110301

ACTIVE INGREDIENTS: Antimony Trisulfide 15 [hp_X]/1 mL; Bryonia Alba Root 15 [hp_X]/1 mL; Oyster Shell Calcium Carbonate, Crude 15 [hp_X]/1 mL; Causticum 15 [hp_X]/1 mL; Solanum Dulcamara Top 15 [hp_X]/1 mL; Graphite 15 [hp_X]/1 mL; Lycopodium Clavatum Spore 15 [hp_X]/1 mL; Mercuric Sulfide 15 [hp_X]/1 mL; Sodium Carbonate 15 [hp_X]/1 mL; Nitric Acid 15 [hp_X]/1 mL; Strychnos Nux-vomica Seed 15 [hp_X]/1 mL; Toxicodendron Pubescens Leaf 15 [hp_X]/1 mL; Juniperus Sabina Leafy Twig 15 [hp_X]/1 mL; Sepia Officinalis Juice 15 [hp_X]/1 mL; Silicon Dioxide 15 [hp_X]/1 mL; Delphinium Staphisagria Seed 15 [hp_X]/1 mL; Sulfur 15 [hp_X]/1 mL; Thuja Occidentalis Leafy Twig 15 [hp_X]/1 mL; Taraxacum Officinale 3 [hp_X]/1 mL
INACTIVE INGREDIENTS: Alcohol

Warts - Moles - Skin Tags

INDICATIONS & USAGE SECTION

Warts - Moles - Skin Tags Formulated for various types of skin conditions such as warts (including genital), moles, keloids, molluscum and skin tags.

DOSAGE & ADMINISTRATION SECTION

Directions: ORAL USE ONLY - SHAKE WELL. Ages 12 and up, take 6 drops orally (ages 0 to 11, give 3 drops) one to four times daily or as directed by a healthcare professional. Sensitive persons begin with 1 drop and gradually increase to full dose.

OTC - ACTIVE INGREDIENT SECTION

Antimon. crud. 15x, Bryonia 15x, Calc.carb. 15x, Causticum 15x, Dulcamara 15x, Graphites 15x, Lycopodium 15x, Merc. sulph. rub. 15x, Nat. carb. 15x, Nitricum ac.15x, Nux vom. 15x, Rhus toxicodendron 15x, Sabina 15x, Sepia 15x, Silicea 15x, Staphysag. 15x, Sulphur 15x, Thuja occ. 15x, Taraxacum 3x, Thuja occ. 3x.

OTC - PURPOSE SECTION

Formulated for various types of skin conditions such as warts (including genital), moles, keloids, molluscum and skin tags.

INACTIVE INGREDIENT SECTION

Inactive Ingredients: USP Purified Water; USP Gluten-free, non-GMO, organic cane dispensing alcohol 20%.

QUESTIONS SECTION

www.newtonlabs.net Newton Laboratories, Inc. FDA Est # 1051203 - Conyers, GA 30012
Questions? 1.800.448.7256

WARNINGS SECTION

Warning: Do not use if tamper - evident seal is broken or missing. Consult a licensed healthcare professional if pregnant, nursing or if symptoms worsen or persist for more than a few days. Keep out of reach of children.

OTC - PREGNANCY OR BREAST FEEDING SECTION

Consult a licensed healthcare professional if pregnant, nursing or if symptoms worsen or persist for more than a few days.

OTC - KEEP OUT OF REACH OF CHILDREN SECTION

Keep out of reach of children.